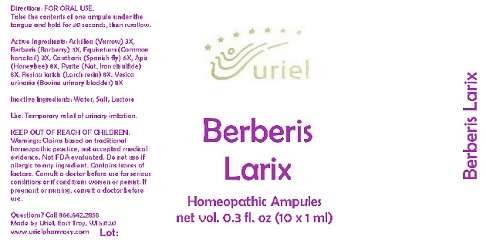 DRUG LABEL: Berberis Larix
NDC: 48951-2042 | Form: LIQUID
Manufacturer: Uriel Pharmacy Inc.
Category: homeopathic | Type: HUMAN OTC DRUG LABEL
Date: 20180521

ACTIVE INGREDIENTS: ACHILLEA MILLEFOLIUM 3 [hp_X]/1 mL; BERBERIS VULGARIS ROOT BARK 3 [hp_X]/1 mL; EQUISETUM ARVENSE TOP 3 [hp_X]/1 mL; LYTTA VESICATORIA 6 [hp_X]/1 mL; APIS MELLIFERA 8 [hp_X]/1 mL; FERROUS DISULFIDE 8 [hp_X]/1 mL; LARIX DECIDUA RESIN 8 [hp_X]/1 mL; SUS SCROFA URINARY BLADDER 8 [hp_X]/1 mL
INACTIVE INGREDIENTS: WATER; SODIUM CHLORIDE; LACTOSE

Berberis Larix

INDICATIONS AND USAGE

Directions: FOR ORAL USE.

DOSAGE AND ADMINISTRATION

Take the contents of one ampule under the tongue and hold for 30 seconds, then swallow.

ACTIVE INGREDIENT

Active Ingredients: Achillea (Yarrow) 3X, Berberis (Barberry) 3X, Equisetum (Common horsetail) 3X, Cantharis (Spanish fly) 6X, Apis (Honeybee) 8X, Pyrite (Nat. Iron disulfide) 8X, Resina laricis (Larch resin) 8X, Vesica urinaria (Bovine urinary bladder) 8X

Inactive Ingredients: Water, Salt, Lactose

PURPOSE

Use: Temporary relief of urinary irritation.

KEEP OUT OF REACH OF CHILDREN.

WARNINGS

Warnings: Claims based on traditional homeopathic practice, not accepted medical evidence. Not FDA evaluated. Do not use if allergic to any ingredient. Contains traces of lactose. Consult a doctor before use for serious conditions or if conditions worsen or persist. If pregnant or nursing, consult a doctor before use.

QUESTIONS

Questions? Call 866.642.2858 Made by Uriel, East Troy, WI 53120 www.urielpharmacy.com